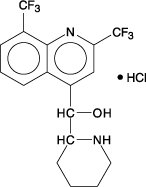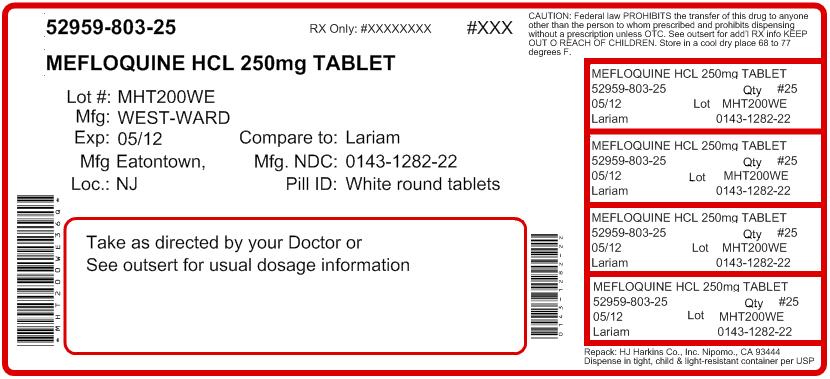 DRUG LABEL: Mefloquine Hydrochloride
NDC: 52959-803 | Form: TABLET
Manufacturer: H.J. Harkins Company, Inc.
Category: prescription | Type: HUMAN PRESCRIPTION DRUG LABEL
Date: 20120216

ACTIVE INGREDIENTS: MEFLOQUINE HYDROCHLORIDE 250 mg/1 1
INACTIVE INGREDIENTS: COLLOIDAL SILICON DIOXIDE; STARCH, CORN; CROSPOVIDONE; LACTOSE MONOHYDRATE; MAGNESIUM STEARATE; CELLULOSE, MICROCRYSTALLINE; POLYSORBATE 80; POVIDONE K30; TALC

Mefloquine Hydrochloride Tablets
Rev. 07/11

DESCRIPTION

Mefloquine Hydrochloride Tablets are an antimalarial agent available as 250-mg tablets of mefloquine hydrochloride (equivalent to 228.0 mg of the free base) for oral administration.

Mefloquine hydrochloride is a 4-quinolinemethanol derivative with the specific chemical name of (R*,S*)-(±)-α-2-piperidinyl-2,8-bis (trifluoromethyl)-4-quinolinemethanol hydrochloride. It is a 2-aryl substituted chemical structural analog of quinine. The drug is a white to almost white crystalline compound, slightly soluble in water.

Mefloquine hydrochloride has a calculated molecular weight of 414.78 and the following structural formula:

Each tablet, for oral administration, contains 250 mg mefloquine hydrochloride and the following inactive ingredients: colloidal silicon dioxide, corn starch, crospovidone, lactose monohydrate, lactose spray dried, magnesium stearate, microcrystalline cellulose, polysorbate 80, polyvinylpyrrolidone and talc.

CLINICAL PHARMACOLOGY

Pharmacokinetics

Absorption

The absolute oral bioavailability of mefloquine has not been determined since an intravenous formulation is not available. The bioavailability of the tablet formation compared with an oral solution was over 85%. The presence of food significantly enhances the rate and extent of absorption, leading to about a 40% increase in bioavailability. In healthy volunteers, plasma concentrations peak 6 to 24 hours (median, about 17 hours) after a single dose of Mefloquine Hydrochloride Tablets. In a similar group of volunteers, maximum plasma concentrations in μg/L are roughly equivalent to the dose in milligrams (for example, a single 1000 mg dose produces a maximum concentration of about 1000 μg/L). In healthy volunteers, a dose of 250 mg once weekly produces maximum steady-state plasma concentrations of 1000 to 2000 μg/L, which are reached after 7 to 10 weeks.

Distribution

In healthy adults, the apparent volume of distribution is approximately 20 L/kg, indicating extensive tissue distribution. Mefloquine may accumulate in parasitized erythrocytes. Experiments conducted in vitro with human blood using concentrations between 50 and 1000 mg/mL showed a relatively constant erythrocyte-to-plasma concentration ratio of about 2 to 1. The equilibrium reached in less than 30 minutes was found to be reversible. Protein binding is about 98%.

Mefloquine crosses the placenta. Excretion into breast milk appears to be minimal (see PRECAUTIONS: Nursing Mothers).

Metabolism

Mefloquine is extensively metabolized in the liver by the cytochrome P450 system. In vitro and in vivo studies strongly suggested that CYP3A4 is the major isoform involved.

Two metabolites of mefloquine have been identified in humans. The main metabolite, 2,8-bis-trifluoromethyl-4-quinoline carboxylic acid, is inactive in Plasmodium falciparum. In a study in healthy volunteers, the carboxylic acid metabolite appeared in plasma 2 to 4 hours after a single oral dose. Maximum plasma concentrations of the metabolite, which were about 50% higher than those of mefloquine, were reached after 2 weeks. Thereafter, plasma levels of the main metabolite and mefloquine declined at a similar rate. The area under the plasma concentration-time curve (AUC) of the main metabolite was 3 to 5 times larger than that of the parent drug. The other metabolite, an alcohol, was present in minute quantities only.

Elimination

In several studies in healthy adults, the mean elimination half-life of mefloquine varied between 2 and 4 weeks, with an average of about 3 weeks. Total clearance, which is essentially hepatic, is in the order of 30 mL/min. There is evidence that mefloquine is excreted mainly in the bile and feces. In volunteers, urinary excretion of unchanged mefloquine and its main metabolite under steady-state condition accounted for about 9% and 4% of the dose, respectively. Concentrations of other metabolites could not be measured in the urine.

Pharmacokinetics in Special Clinical Situations

Children and the Elderly

No relevant age-related changes have been observed in the pharmacokinetics of mefloquine. Therefore, the dosage for children has been extrapolated from the recommended adult dose.

No pharmacokinetic studies have been performed in patients with renal insufficiency since only a small proportion of the drug is eliminated renally. Mefloquine and its main metabolite are not appreciably removed by hemodialysis. No special chemoprophylactic dosage adjustments are indicated for dialysis patients to achieve concentrations in plasma similar to those in healthy persons.

Although clearance of mefloquine may increase in late pregnancy, in general, pregnancy has no clinically relevant effect on the pharmacokinetics of mefloquine.

The pharmacokinetics of mefloquine may be altered in acute malaria.

Pharmacokinetic differences have been observed between various ethnic populations. In practice, however, these are of minor importance compared with host immune status and sensitivity of the parasite.

During long-term prophylaxis (>2 years), the trough concentrations and the elimination half-life of mefloquine were similar to those obtained in the same population after 6 months of drug use, which is when they reached steady state.

In vitro and in vivo studies showed no hemolysis associated with glucose-6-phosphate dehydrogenase deficiency (see ANIMAL TOXICOLOGY).

Microbiology

Mechanism of Action

Mefloquine is an antimalarial agent which acts as a blood schizonticide. Its exact mechanism of action is not known.

Activity In Vitro and In Vivo

Mefloquine is active against the erythrocytic stages of Plasmodium species (See INDICATIONS AND USAGE). However, the drug has no effect against the exoerythrocytic (hepatic) stages of the parasite. Mefloquine is effective against malaria parasites resistant to chloroquine (see INDICATIONS AND USAGE).

Drug Resistance

Strains of P. falciparum with decreased susceptibility to mefloquine can be selected in vitro or in vivo. Resistance of P. falciparum to mefloquine has been reported in areas of multi-drug resistance in South East Asia. Increased incidences of resistance have also been reported in other parts of the world.

Cross Resistance

Cross-resistance between mefloquine and halofantrine and cross-resistance between mefloquine and quinine have been observed in some regions.

INDICATIONS AND USAGE

Treatment of Acute Malaria Infections

Mefloquine Hydrochloride Tablets are indicated for the treatment of mild to moderate acute malaria caused by mefloquine-susceptible strains of P. falciparum (both chloroquine-susceptible and resistant strains) or by Plasmodium vivax. There are insufficient clinical data to document the effect of mefloquine in malaria caused by P. ovale or P. malariae.

- Note: Patients with acute P. vivax malaria, treated with Mefloquine Hydrochloride Tablets, are at high risk of relapse because Mefloquine Hydrochloride Tablets do not eliminate exoerythrocytic (hepatic phase) parasites. To avoid relapse, after initial treatment of the acute infection with mefloquine, patients should subsequently be treated with an 8-aminoquinoline derivative (e.g., primaquine).

Prevention of Malaria

Mefloquine Hydrochloride Tablets are indicated for the prophylaxis of P. falciparum and P. vivax malaria infections, including prophylaxis of chloroquine-resistant strains of P. falciparum.

CONTRAINDICATIONS

Use of Mefloquine Hydrochloride Tablets is contraindicated in patients with a known hypersensitivity to mefloquine or related compounds (e.g., quinine and quinidine) or to any of the excipients contained in the formulation. Mefloquine Hydrochloride Tablets should not be prescribed for prophylaxis in patients with active depression, a recent history of depression, generalized anxiety disorder, psychosis, or schizophrenia or other major psychiatric disorders, or with a history of convulsions.

WARNINGS

In case of life-threatening, serious or overwhelming malaria infections due to P. falciparum, patients should be treated with an intravenous antimalarial drug. Following completion of intravenous treatment, Mefloquine Hydrochloride Tablets may be given to complete the course of therapy.

Halofantrine should not be administered with Mefloquine Hydrochloride Tablets or within 15 weeks of the last dose of Mefloquine Hydrochloride Tablets due to the risk of a potentially fatal prolongation of the QTc interval (see CLINICAL PHARMACOLOGY: Pharmacokinetics: Elimination).

Ketoconazole should not be administered with Mefloquine Hydrochloride Tablets or within 15 weeks of the last dose of Mefloquine Hydrochloride Tablets due to the risk of a potentially fatal prolongation of the QTc interval. Ketoconazole increases plasma concentrations and elimination half-life of mefloquine following co-administration (see CLINICAL PHARMACOLOGY: Pharmacokinetics: Elimination and PRECAUTIONS: Drug Interactions).

Mefloquine may cause psychiatric symptoms in a number of patients, ranging from anxiety, paranoia, and depression to hallucinations and psychotic behavior. On occasions, these symptoms have been reported to continue long after mefloquine has been stopped. Rare cases of suicidal ideation and suicide have been reported though no relationship to drug administration has been confirmed. To minimize the chances of these adverse events, mefloquine should not be taken for prophylaxis in patients with active depression or with a recent history of depression, generalized anxiety disorder, psychosis, or schizophrenia or other major psychiatric disorders. Mefloquine Hydrochloride Tablets should be used with caution in patients with a previous history of depression.

During prophylactic use, if psychiatric symptoms such as acute anxiety, depression, restlessness or confusion occur, these may be considered prodromal to a more serious event. In these cases, the drug must be discontinued and an alternative medication should be substituted.

Concomitant administration of Mefloquine Hydrochloride Tablets and quinine or quinidine may produce electrocardiographic abnormalities.

Concomitant administration of Mefloquine Hydrochloride Tablets and quinine or chloroquine may increase the risk of convulsions.

PRECAUTIONS

Hypersensitivity Reactions

Hypersensitivity reactions ranging from mild cutaneous events to anaphylaxis cannot be predicted. In patients with epilepsy, Mefloquine Hydrochloride Tablets may increase the risk of convulsions. The drug should therefore be prescribed only for curative treatment in such patients and only if there are compelling medical reasons for its use (see PRECAUTIONS: Drug Interactions).

Central and Peripheral Nervous System Effects

Caution should be exercised with regard to activities requiring alertness and fine motor coordination such as driving, piloting aircraft, operating machinery, and deep-sea diving, as dizziness or vertigo, a loss of balance, or other disorders of the central or peripheral nervous system have been reported during and following the use of Mefloquine Hydrochloride Tablets. Because of the long half-life of mefloquine, adverse reactions to mefloquine may occur or persist up to several weeks after discontinuation of the drug. In a small number of patients, dizziness or vertigo and loss of balance have been reported to continue for months after discontinuation of the drug (see ADVERSE REACTIONS: Postmarketing).

Mefloquine Hydrochloride Tabletsshould be used with caution in patients with psychiatric disturbances because mefloquine use has been associated with emotional disturbances (see ADVERSE REACTIONS).

Use in Patients with Hepatic Impairment

In patients with impaired liver function the elimination of mefloquine may be prolonged, leading to higher plasma levels and a higher risk of adverse reactions.

Long-Term Use

This drug has been administered for longer than one year. If the drug is to be administered for a prolonged period, periodic evaluations including liver function tests should be performed.

Although retinal abnormalities seen in humans with long-term chloroquine use have not been observed with mefloquine use, long-term feeding of mefloquine to rats resulted in dose-related ocular lesions (retinal degeneration, retinal edema and lenticular opacity at 12.5 mg/kg/day and higher) (see ANIMAL TOXICOLOGY). Therefore, periodic ophthalmic examinations are recommended.

Cardiac Effects

Parenteral studies in animals show that mefloquine, a myocardial depressant, possesses 20% of the anti-fibrillatory action of quinidine and produces 50% of the increase in the PR interval reported with quinine. The effect of mefloquine on the compromised cardiovascular system has not been evaluated. However, transitory and clinically silent ECG alterations have been reported during the use of mefloquine. Alterations included sinus bradycardia, sinus arrhythmia, first degree AV-block, prolongation of the QTc interval and abnormal T waves (see also cardiovascular effects under PRECAUTIONS: Drug Interactions and ADVERSE REACTIONS). The benefits of Mefloquine Hydrochloride Tablets therapy should be weighed against the possibility of adverse effects in patients with cardiac disease.

Drug Resistance and Cross-Resistance

Geographical drug resistance patterns of P. falciparum occur and the preferred choice of malaria prophylaxis might be different from one area to another. For example, resistance of P. falciparum to mefloquine has been reported, predominately in areas of multi-drug resistance in South-East Asia. Cross-resistance between mefloquine and halofantrine and cross-resistance between mefloquine and quinine have been observed in some regions. For current advice on geographical resistance patterns competent national expert centers should be consulted.

Agranulocytosis and Aplastic Anemia

Cases of agranulocytosis and aplastic anemia have been reported during Mefloquine Hydrochloride Tablets therapy (see ADVERSE REACTIONS).

Laboratory Tests

Periodic evaluation of hepatic function should be performed during prolonged prophylaxis.

Information for Patients

Medication Guide: As required by law, a Mefloquine Hydrochloride Tablets Medication Guide is supplied to patients when Mefloquine Hydrochloride Tablets are dispensed. An information wallet card is also supplied to patients when Mefloquine Hydrochloride Tablets are dispensed. Patients should be instructed to read the Medication Guide when mefloquine is received and to carry the information wallet card with them when they are taking Mefloquine Hydrochloride Tablets. The complete texts of the Medication Guide and information wallet card are reprinted at the end of this document.

Patients should be advised:

- that malaria can be a life-threatening infection in the traveler;
- that Mefloquine Hydrochloride Tablets are being prescribed to help prevent or treat this serious infection;
- that in a small percentage of cases, patients are unable to take this medication because of side effects, including dizziness or vertigo and loss of balance, and it may be necessary to change medications. Although side effects of dizziness or vertigo and loss of balance are usually mild and do not cause people to stop taking the medication, in a small number of patients it has been reported that these symptoms may continue for months after discontinuation of the drug;
- that when used as prophylaxis, the first dose of Mefloquine Hydrochloride Tablets should be taken one week prior to arrival in an endemic area;
- that if the patients experience psychiatric symptoms such as acute anxiety, depression, restlessness or confusion, these may be considered prodromal to a more serious event. In these cases, the drug must be discontinued and an alternative medication should be substituted;
- that no chemoprophylactic regimen is 100% effective, and protective clothing, insect repellents, and bednets are important components of malaria prophylaxis;
- to seek medical attention for any febrile illness that occurs after return from a malarious area and to inform their physician that they may have been exposed to malaria.

Drug Interactions

Drug-drug interactions with Mefloquine Hydrochloride Tablets have not been explored in detail. There is one report of cardiopulmonary arrest, with full recovery, in a patient who was taking a beta blocker (propranolol) (see PRECAUTIONS: Cardiac Effects). The effects of mefloquine on the compromised cardiovascular system have not been evaluated. The benefits of mefloquine therapy should be weighed against the possibility of adverse effects in patients with cardiac disease.

Halofantrine and Other Antimalarials

Halofantrine should not be administered with Mefloquine Hydrochloride Tablets or within 15 weeks of the last dose of Mefloquine Hydrochloride Tablets due to the risk of a potentially fatal prolongation of the QTc interval (see WARNINGS).

Concomitant administration of Mefloquine Hydrochloride Tablets and other related antimalarial compounds (e.g., quinine, quinidine and chloroquine) may produce electrocardiographic abnormalities and increase the risk of convulsions (see WARNINGS). If these drugs are to be used in the initial treatment of severe malaria, Mefloquine Hydrochloride Tablets administration should be delayed at least 12 hours after the last dose. Clinically significant QTc prolongation has not been found with mefloquine alone.

Ketoconazole (Potent Inhibitor of CYP3A4)

Co-administration of a single 500 mg oral dose of Mefloquine Hydrochloride Tablets with 400 mg of ketoconazole once daily for 10 days in 8 healthy volunteers resulted in an increase in the mean Cmax and AUC of mefloquine by 64% and 79%, respectively, and an increase in the mean elimination half-life of mefloquine from 322 hours to 448 hours. Ketoconazole should not be administered with Mefloquine Hydrochloride Tablets or within 15 weeks of the last dose of Mefloquine Hydrochloride Tablets due to the risk of a potentially fatal prolongation of the QTc interval (see WARNINGS).

Other Drugs that Prolong the QTc Interval

Co-administration of other drugs known to alter cardiac conduction (e.g., anti-arrhythmic or beta-adrenergic blocking agents, calcium channel blockers, antihistamines or H1-blocking agents, tricyclic antidepressants and phenothiazines) might also contribute to a prolongation of the QTc interval. There are no data that conclusively establish whether the concomitant administration of mefloquine and the above listed agents has an effect on cardiac function.

Anticonvulsants

In patients taking an anticonvulsant (e.g., valproic acid, carbamazepine, phenobarbital or phenytoin), the concomitant use of Mefloquine Hydrochloride Tablets may reduce seizure control by lowering the plasma levels of the anticonvulsant. Therefore, patients concurrently taking antiseizure medication and Mefloquine Hydrochloride Tablets should have the blood level of their antiseizure medication monitored and the dosage adjusted appropriately (see PRECAUTIONS).

Vaccines

When Mefloquine Hydrochloride Tablets are taken concurrently with oral live typhoid vaccines, attenuation of immunization cannot be excluded. Vaccinations with attenuated live bacteria should therefore be completed at least 3 days before the first dose of Mefloquine Hydrochloride Tablets.

Rifampin (Potent Inducer of CYP3A4)

Co-administration of a single 500 mg oral dose of Mefloquine Hydrochloride Tablets and 600 mg of rifampin once daily for 7 days in 7 healthy Thai volunteers resulted in a decrease in the mean Cmax and AUC of mefloquine by 19% and 68%, respectively, and a decrease in the mean elimination half-life of mefloquine from 305 hours to 113 hours. Rifampin should be used cautiously in patients taking Mefloquine Hydrochloride Tablets .

Inhibitors and Inducers of CYP3A4

Mefloquine does not inhibit or induce the CYP 450 enzyme system. Thus, concomitant administration of Mefloquine Hydrochloride Tablets and substrates of the CYP 450 enzyme system is not expected to result in a drug interaction. However, mefloquine is metabolized by CYP3A4 and inhibitors of CYP3A4 may modify the pharmacokinetics/metabolism of mefloquine, leading to an increase in mefloquine plasma concentrations and potential risk of adverse reactions. Therefore, Mefloquine Hydrochloride Tablets should be used with caution when administered concomitantly with CYP3A4 inhibitors. Similarly, inducers of CYP3A4 may modify the pharmacokinetics/metabolism of mefloquine, leading to a decrease in mefloquine plasma concentrations and potential reduction in efficacy of Mefloquine Hydrochloride Tablets. Therefore, Mefloquine Hydrochloride Tablets should also be used with caution when administered concomitantly with CYP3A4 inducers.

Substrates and Inhibitors of P-glycoprotein

It has been shown in vitro that mefloquine is a substrate and an inhibitor of P-glycoprotein. Therefore, drug-drug interactions could also occur with drugs that are substrates or are known to modify the expression of this transporter. The clinical relevance of these interactions is not known to date.

Other Potential Interactions

No other drug interactions are known. Nevertheless, the effects of Mefloquine Hydrochloride Tablets on travelers receiving comedication, particularly diabetics or patients using anticoagulants, should be checked before departure.

In clinical trials, the concomitant administration of sulfadoxine and pyrimethamine did not alter the adverse reaction profile of mefloquine.

Carcinogenesis, Mutagenesis, Impairment of Fertility

Carcinogenesis

The carcinogenic potential of mefloquine was studied in rats and mice in 2-year feeding studies at doses of up to 30 mg/kg/day. No treatment-related increases in tumors of any type were noted.

Mutagenesis

The mutagenic potential of mefloquine was studied in a variety of assay systems including: Ames test, a host-mediated assay in mice, fluctuation tests and a mouse micronucleus assay. Several of these assays were performed with and without prior metabolic activation. In no instance was evidence obtained for the mutagenicity of mefloquine.

Impairment of Fertility

Fertility studies in rats at doses of 5, 20, and 50 mg/kg/day of mefloquine have demonstrated adverse effects on fertility in the male at the high dose of 50 mg/kg/day, and in the female at doses of 20 and 50 mg/kg/day. Histopathological lesions were noted in the epididymides from male rats at doses of 20 and 50 mg/kg/day. Administration of 250 mg/week of mefloquine (base) in adult males for 22 weeks failed to reveal any deleterious effects on human spermatozoa.

Pregnancy

Pregnancy Category B

Data from published studies in pregnant women have shown no increase in the risk of teratogenic effects or adverse pregnancy outcomes following mefloquine treatment or prophylaxis during pregnancy. Reproduction studies in mice, rats and rabbits have shown teratogenic effects at doses similar to the clinical acute treatment dose in humans. Despite the animal findings, it would appear that the possibility of fetal harm is remote, if the drug is used during pregnancy. Nevertheless, because the studies in humans cannot rule out the possibility of harm, mefloquine should be used during pregnancy only if clearly needed.

Published data on mefloquine use during pregnancy include randomized controlled trials, intervention trials, prospective and retrospective cohort studies, and case series. These data showed that pregnant women who took mefloquine at various doses for both prevention and treatment of malaria did not have an increased risk of teratogenic effects or adverse pregnancy outcomes compared to the background rate in the general population. These data include more than 700 exposures to mefloquine in the first trimester of pregnancy and over 2,000 exposures in the second and third trimester.

Mefloquine administered to pregnant mice, rats, and rabbits was teratogenic at doses similar to the clinical acute treatment dose of 21 to 25 mg/kg, based on body surface area comparisons. In all three animal species, CNS effects (e.g., exencephaly, hydrocephaly or partially missing medulla oblongata) and craniofacial malformations were observed. At the same doses, mefloquine was also embryotoxic in mice and rabbits. All of these findings were observed at doses that were maternally toxic.

Nursing Mothers

Mefloquine is excreted in human milk in small amounts, the activity of which is unknown. Based on a study in a few subjects, low concentrations (3% to 4%) of mefloquine were excreted in human milk following a dose equivalent to 250 mg of the free base. Caution should be exercised when administered to a nursing woman.

Pediatric Use

Use of Mefloquine Hydrochloride Tablets to treat acute, uncomplicated P. falciparum malaria in pediatric patients is supported by evidence from adequate and well-controlled studies of Mefloquine Hydrochloride Tablets in adults with additional data from published open-label and comparative trials using Mefloquine Hydrochloride Tablets to treat malaria caused by P. falciparum in patients younger than 16 years of age. The safety and effectiveness of Mefloquine Hydrochloride Tablets for the treatment of malaria in pediatric patients below the age of 6 months have not been established.

In several studies, the administration of Mefloquine Hydrochloride Tablets for the treatment of malaria was associated with early vomiting in pediatric patients. Early vomiting was cited in some reports as a possible cause of treatment failure. If a second dose is not tolerated, the patient should be monitored closely and alternative malaria treatment considered if improvement is not observed within a reasonable period of time (see DOSAGE AND ADMINISTRATION).

Geriatric Use

Clinical studies of Mefloquine Hydrochloride Tablets did not include sufficient numbers of subjects aged 65 and over to determine whether they respond differently from younger subjects. Other reported clinical experience has not identified differences in responses between the elderly and younger patients. Since electrocardiographic abnormalities have been observed in individuals treated with Mefloquine Hydrochloride Tablets (see PRECAUTIONS) and underlying cardiac disease is more prevalent in elderly than in younger patients, the benefits of Mefloquine Hydrochloride Tablets therapy should be weighed against the possibility of adverse cardiac effects in elderly patients.

ADVERSE REACTIONS

Clinical

At the doses used for treatment of acute malaria infections, the symptoms possibly attributable to drug administration cannot be distinguished from those symptoms usually attributable to the disease itself.

Among subjects who received mefloquine for prophylaxis of malaria, the most frequently observed adverse experience was vomiting (3%). Dizziness, syncope, extrasystoles and other complaints affecting less than 1% were also reported.

Among subjects who received mefloquine for treatment, the most frequently observed adverse experiences included: dizziness, myalgia, nausea, fever, headache, vomiting, chills, diarrhea, skin rash, abdominal pain, fatigue, loss of appetite, and tinnitus. Those side effects occurring in less than 1% included bradycardia, hair loss, emotional problems, pruritus, asthenia, transient emotional disturbances and telogen effluvium (loss of resting hair). Seizures have also been reported.

Two serious adverse reactions were cardiopulmonary arrest in one patient shortly after ingesting a single prophylactic dose of mefloquine while concomitantly using propranolol (see PRECAUTIONS: Drug Interactions), and encephalopathy of unknown etiology during prophylactic mefloquine administration. The relationship of encephalopathy to drug administration could not be clearly established.

Laboratory

The most frequently observed laboratory alterations which could be possibly attributable to drug administration were decreased hematocrit, transient elevation of transaminases, leukopenia and thrombocytopenia. These alterations were observed in patients with acute malaria who received treatment doses of the drug and were attributed to the disease itself.

During prophylactic administration of mefloquine to indigenous populations in malaria-endemic areas, the following occasional alterations in laboratory values were observed: transient elevation of transaminases, leukocytosis or thrombocytopenia.

Because of the long half-life of mefloquine, adverse reactions to Mefloquine Hydrochloride Tablets may occur or persist up to several weeks after discontinuation of the drug.

Postmarketing

Postmarketing surveillance indicates that the same kind of adverse experiences are reported during prophylaxis, as well as acute treatment. Because these experiences are reported voluntarily from a population of uncertain size, it is not always possible to reliably estimate their frequency or establish a causal relationship to Mefloquine Hydrochloride Tablets exposure.

The most frequently reported adverse events are nausea, vomiting, loose stools or diarrhea, abdominal pain, dizziness or vertigo, loss of balance, and neuropsychiatric events such as headache, somnolence, and sleep disorders (insomnia, abnormal dreams). These are usually mild and may decrease despite continued use. In a small number of patients it has been reported that dizziness or vertigo and loss of balance may continue for months after discontinuation of the drug.

Occasionally, more severe neuropsychiatric disorders have been reported such as: sensory and motor neuropathies (including paresthesia, tremor and ataxia), convulsions, agitation or restlessness, anxiety, depression, mood swings, panic attacks, memory impairment, confusion, hallucinations, aggression, psychotic or paranoid reactions and encephalopathy. Rare cases of suicidal ideation and suicide have been reported though no relationship to drug administration has been confirmed.

Other less frequently reported adverse events include:

Cardiovascular Disorders: circulatory disturbances (hypotension, hypertension, flushing, syncope), chest pain, tachycardia or palpitation, bradycardia, irregular heart rate, extrasystoles, A-V block, and other transient cardiac conduction alterations

Skin Disorders: rash, exanthema, erythema, urticaria, pruritus, edema, hair loss, erythema multiforme, and Stevens-Johnson syndrome

Musculoskeletal Disorders: muscle weakness, muscle cramps, myalgia, and arthralgia

Respiratory Disorders: dyspnea, pneumonitis of possible allergic etiology

Hepatobiliary Disorders: drug-related hepatic disorders from asymptomatic transient transaminase elevations to hepatic failure drug-related hepatic disorders from asymptomatic transient transaminase elevations to hepatic failure

Blood and Lymphatic System Disorders: agranulocytosis, aplastic anemia agranulocytosis, aplastic anemia

Other Symptoms: visual disturbances, vestibular disorders including tinnitus and hearing impairment, asthenia, malaise, fatigue, fever, hyperhidrosis, chills, dyspepsia and loss of appetite

To report SUSPECTED ADVERSE REACTIONS, contact West-ward Pharmaceutical Corp. at 1-877-233- 2001, and the FDA at 1-800-FDA-1088 or www.fda.gov/medwatch.

OVERDOSAGE

Symptoms and Signs

In cases of overdosage with Mefloquine Hydrochloride Tablets, the symptoms mentioned under ADVERSE REACTIONS may be more pronounced.

Treatment

Patients should be managed by symptomatic and supportive care following Mefloquine Hydrochloride Tablets overdose. There are no specific antidotes. Monitor cardiac function (if possible by ECG) and neuropsychiatric status for at least 24 hours. Provide symptomatic and intensive supportive treatment as required, particularly for cardiovascular disturbances.

DOSAGE AND ADMINISTRATION

(see INDICATIONS AND USAGE)

Adult Patients

Treatment of mild to moderate malaria in adults caused by P. vivax or mefloquine-susceptible strains of P. falciparum

Five tablets (1250 mg) mefloquine hydrochloride to be given as a single oral dose. The drug should not be taken on an empty stomach and should be administered with at least 8 oz (240 mL) of water.

If a full-treatment course with Mefloquine Hydrochloride Tablets does not lead to improvement within 48 to 72 hours, Mefloquine Hydrochloride Tablets should not be used for retreatment. An alternative therapy should be used. Similarly, if previous prophylaxis with mefloquine has failed, Mefloquine Hydrochloride Tablets should not be used for curative treatment.

- Note: Patients with acute P. vivax malaria, treated with Mefloquine Hydrochloride Tablets, are at high risk of relapse because Mefloquine Hydrochloride Tablets do not eliminate exoerythrocytic (hepatic phase) parasites. To avoid relapse after initial treatment of the acute infection with Mefloquine Hydrochloride Tablets, patients should subsequently be treated with an 8-aminoquinoline derivative (e.g., primaquine).

Malaria Prophylaxis

One 250 mg Mefloquine Hydrochloride Tablet once weekly.

Prophylactic drug administration should begin 1 week before arrival in an endemic area. Subsequent weekly doses should be taken regularly, always on the same day of each week, preferably after the main meal. To reduce the risk of malaria after leaving an endemic area, prophylaxis must be continued for 4 additional weeks to ensure suppressive blood levels of the drug when merozoites emerge from the liver. Tablets should not be taken on an empty stomach and should be administered with at least 8 oz (240 mL) of water.

In certain cases, e.g., when a traveler is taking other medication, it may be desirable to start prophylaxis 2 to 3 weeks prior to departure, in order to ensure that the combination of drugs is well tolerated (see PRECAUTIONS: Drug Interactions).

When prophylaxis with Mefloquine Hydrochloride Tablets fails, physicians should carefully evaluate which antimalarial to use for therapy.

Pediatric Patients

Treatment of mild to moderate malaria in pediatric patients caused by mefloquine-susceptible strains of P. falciparum

Twenty (20) to 25 mg/kg body weight. Splitting the total therapeutic dose into 2 doses taken 6 to 8 hours apart may reduce the occurrence or severity of adverse effects. Experience with Mefloquine Hydrochloride Tablets in pediatric patients weighing less than 20 kg is limited. The drug should not be taken on an empty stomach and should be administered with ample water. The tablets may be crushed and suspended in a small amount of water, milk or other beverage for administration to small children and other persons unable to swallow them whole.

If a full-treatment course with Mefloquine Hydrochloride Tablets does not lead to improvement within 48 to 72 hours, Mefloquine Hydrochloride Tablets should not be used for retreatment. An alternative therapy should be used. Similarly, if previous prophylaxis with mefloquine has failed, Mefloquine Hydrochloride Tablets should not be used for curative treatment.

In pediatric patients, the administration of Mefloquine Hydrochloride Tablets for the treatment of malaria has been associated with early vomiting. In some cases, early vomiting has been cited as a possible cause of treatment failure (see PRECAUTIONS). If a significant loss of drug product is observed or suspected because of vomiting, a second full dose of Mefloquine Hydrochloride Tablets should be administered to patients who vomit less than 30 minutes after receiving the drug. If vomiting occurs 30 to 60 minutes after a dose, an additional half-dose should be given. If vomiting recurs, the patient should be monitored closely and alternative malaria treatment considered if improvement is not observed within a reasonable period of time.

The safety and effectiveness of Mefloquine Hydrochloride Tablets to treat malaria in pediatric patients below the age of 6 months have not been established.

Malaria Prophylaxis

The recommended prophylactic dose of Mefloquine Hydrochloride Tablets is approximately 5 mg/kg body weight once weekly. One 250 mg Mefloquine Hydrochloride Tablet should be taken once weekly in pediatric patients weighing over 45 kg. In pediatric patients weighing less than 45 kg, the weekly dose decreases in proportion to body weight:

30 to 45 kg: 3/4 tablet
20 to 30 kg: 1/2 tablet

Experience with Mefloquine Hydrochloride Tablets in pediatric patients weighing less than 20 kg is limited.

HOW SUPPLIED

Mefloquine Hydrochloride Tablets 250 mg, are supplied as White Round Scored Tablets, Debossed 'WW 282' and available in:

Bottles of 25 tablets.

Storage

Store at 20-25°C (68-77°F) [See USP Controlled Room Temperature]. Protect from light and moisture.

Dispense in a tight, light-resistant container as defined in the USP using a child-resistant closure.

Manufactured by:
West-ward Pharmaceutical Corp.
Eatontown, NJ 07724
Revised July 2011

ANIMAL TOXICOLOGY

Ocular lesions were observed in rats fed mefloquine daily for 2 years. All surviving rats given 30 mg/kg/day had ocular lesions in both eyes characterized by retinal degeneration, opacity of the lens, and retinal edema. Similar but less severe lesions were observed in 80% of female and 22% of male rats fed 12.5 mg/kg/day for 2 years. At doses of 5 mg/kg/day, only corneal lesions were observed. They occurred in 9% of rats studied.

Revised 07/11

MEDICATION GUIDE

Read this entire Medication Guide before you start taking Mefloquine Hydrochloride Tablets and each time you get a refill. There may be new information. This information does not take the place of talking to your doctor about your medical condition or your treatment.

What is the most important information I should know about Mefloquine Hydrochloride Tablets?

Your doctor or pharmacist will give you an Information Wallet Card along with this Medication Guide. It has important information about Mefloquine Hydrochloride Tablets and should be carried with you at all times while you take Mefloquine Hydrochloride Tablets.

Mefloquine Hydrochloride Tablets can cause serious mental problems.

- Some people who take mefloquine have sudden serious mental problems, including:
  - severe anxiety
  - paranoia (feelings of mistrust towards others)
  - hallucinations (seeing or hearing things that are not there)
  - depression
  - feeling restless
  - unusual behavior
  - feeling confused

In some patients these serious side effects can go on after Mefloquine is stopped.

- Some people who take Mefloquine Hydrochloride Tablets think about suicide (putting an end to their life). Some people who were taking Mefloquine Hydrochloride Tablets committed suicide. It is not known whether Mefloquine Hydrochloride Tablets were responsible for those suicides.
  If you have any of these serious mental problems, or you develop other serious side effects or mental problems, you should call your doctor right away as it may be necessary to stop taking Mefloquine Hydrochloride Tablets and use another medicine to prevent malaria.
  You need to take malaria prevention medicine before you travel to a malaria area, while you are in a malaria area, and after you return from a malaria area.
  If you are told by a doctor to stop taking Mefloquine Hydrochloride Tablets because of the side effects or for other reasons, you will need to take another malaria medicine.
  If you do not have access to a doctor or to another medicine and have to stop taking Mefloquine Hydrochloride Tablets, leave the malaria area and contact a doctor as soon as possible because leaving the malaria area may not protect you from getting malaria. You will still need to take a malaria prevention medicine for another 4 weeks.
- Do not take halofantrine (used to treat malaria) or ketoconazole (used for fungal infections) with Mefloquine Hydrochloride Tablets or within 15 weeks of your last dose of Mefloquine Hydrochloride Tablets. You may have serious heart problems that can lead to death. Do not take quinine (Qualaquin) or quinidine (used to treat malaria or irregular heart beat) with Mefloquine Hydrochloride Tablets. You may have serious heart problems.
- Do not take quinine (Qualaquin) or chloroquine (Aralen) (used to treat malaria) with Mefloquine Hydrochloride Tablets. You may have a greater risk for convulsions (seizures).

What are Mefloquine Hydrochloride Tablets?

Mefloquine Hydrochloride Tablets are a prescription medicine used to prevent and treat malaria. Malaria can be a life-threatening infection. Mefloquine does not work for all types of malaria.

It is not known if Mefloquine Hydrochloride Tablets are safe and effective in children under 6 months old for the treatment of malaria.

It is not known how well Mefloquine Hydrochloride Tablets work to prevent malaria in infants weighing less than 44 lbs (20 kg).

Who should not take Mefloquine Hydrochloride Tablets?

Do not take Mefloquine Hydrochloride Tablets if you have:

- depression or had depression recently
- had recent mental problems, including anxiety disorder, schizophrenia, or psychosis (losing touch with reality)
- seizures or had seizures (epilepsy or convulsions)
- an allergy to quinine, quinidine, mefloquine or any ingredients in mefloquine. See the end of this Medication Guide for a complete list of ingredients in mefloquine.

Talk to your doctor before you take Mefloquine Hydrochloride Tablets if you have any of the conditions listed above.

What should I tell my doctor before taking Mefloquine Hydrochloride Tablets?

Before taking Mefloquine Hydrochloride Tablets, tell your doctor about all your medical conditions, including if you have:

- heart disease
- liver problems
- seizures or epilepsy
- diabetes
- blood clotting problems or take blood thinner medicines (anticoagulants)
- mental problems
- are pregnant or plan to become pregnant. It is not known if mefloquine will harm your unborn baby. Talk to you doctor if you are pregnant or plan to become pregnant.
- use birth control while you take mefloquine and for 3 months after you stop mefloquine. If you have an unplanned pregnancy, talk to your doctor right away.
- are breast-feeding or plan to breast-feed. Mefloquine can pass through your milk and may harm your baby. Ask your doctor whether you will need to stop breast-feeding or use another medicine.

After leaving a malaria area, if you have a fever contact your doctor right away.

Tell your doctor about all the medicines you take, including prescription and nonprescription medicines, vitamins, and herbal supplements. Mefloquine Hydrochloride Tablets and other medicines may affect each other causing side effects.

Know the medicines you take. Keep a list of them and show it to your doctor and pharmacist when you get a new medicine.

Especially tell your doctor if you take:

- ketoconazole used to treat fungal infections
- halofantrine, quinine (Qualaquin), quinidine, chloroquine (Aralen) or other medicines used to treat malaria
- anti-arrhythmic medicines, beta-adrenergic blocking medicines and calcium channel blockers used to treat heart problems or high blood pressure
- antihistamines or H1-blocking agents used to treat allergies
- tricyclic antidepressants used to treat depression
- phenothiazines used to treat mental problems
- anticonvulsants used to treat seizures
- vaccines containing live bacteria. Your doctor may want you to finish receiving your vaccines at least 3 days before you start mefloquine.
- rifampin and rifampin-containing products (Rifadin, Rifamate, Rifater, Rimactane) used to treat infections

Ask your doctor or pharmacist for a list of these medicines if you are not sure.

How should I take Mefloquine Hydrochloride Tablets?

- Take Mefloquine Hydrochloride Tablets exactly as your doctor tells you to take it. Your doctor will tell you how many Mefloquine Hydrochloride Tablets to take and when to take them.
- You will start taking Mefloquine Hydrochloride Tablets to prevent malaria between 1 to 3 weeks before you travel to a malaria area.
- Take Mefloquine Hydrochloride Tablets just after eating your main meal and with at least one cup (8 ounces) of water.
- Do not take Mefloquine Hydrochloride Tablets on an empty stomach.
- If you vomit after taking Mefloquine Hydrochloride Tablets, call your healthcare provider to see if you should take another dose.
- Continue taking Mefloquine Hydrochloride Tablets for 4 weeks after returning from a malaria area.
- Mefloquine Hydrochloride Tablets may be crushed and mixed with a small amount of water, milk or other beverage for children or other people unable to swallow Mefloquine Hydrochloride Tablets whole. Your doctor will tell you the correct dose for your child based on your child’s weight.
- If you take Mefloquine Hydrochloride Tablets for a year or longer, your doctor should check your
  - eyes, especially if you have trouble seeing while you take Mefloquine Hydrochloride Tablets
  - liver function to see if there has been damage to your liver
  - Use protective clothing, insect repellents, and bednets to protect you from being bitten by mosquitoes. Medicine alone does not always stop you from catching malaria from mosquito bites.

What should I avoid while taking Mefloquine Hydrochloride Tablets?

Avoid activities such as driving a car or using heavy machinery or other activities needing alertness and careful movements (fine motor coordination) until you know how mefloquine affects you. You may feel dizzy or lose your balance. This could happen for months after you stop taking mefloquine. See “What are the possible side effects of mefloquine?”

What are the possible side effects of Mefloquine Hydrochloride Tablets?

Also see “What is the most important information I should know about Mefloquine Hydrochloride Tablets?”

Mefloquine Hydrochloride Tablets may cause serious side effects, including:

- convulsions (seizures)
- liver problems
- heart problems

The most common side effects of Mefloquine Hydrochloride Tablets include:

- nausea
- vomiting
- diarrhea
- abdominal pain
- dizziness or loss of balance (vertigo), which may continue for months after mefloquine is stopped
- headache
- sleeping problems (sleepiness, unable to sleep, bad dreams)

The most common side effects in people who take Mefloquine Hydrochloride Tablets for treatment include:

- muscle pain
- fever
- chills
- skin rash
- fatigue
- loss of appetite
- ringing in the ears
- irregular heart beat

Tell your doctor if you have any side effect that bothers you or that does not go away. These are not all the possible side effects of Mefloquine Hydrochloride Tablets. For more information, ask your doctor or pharmacist.

Call your doctor for medical advice about side effects. You may report side effects to FDA at 1-800-FDA-1088.

How should I store Mefloquine Hydrochloride Tablets?

- Store Mefloquine Hydrochloride Tablets between 59ºF to 86ºF (15ºC to 30ºC)
- Safely throw away medicine that is out of date or no longer needed.

Keep Mefloquine Hydrochloride Tablets and all medicines out of the reach of children.

General information about the safe and effective use of Mefloquine Hydrochloride Tablets.

Medicines are sometimes prescribed for purposes other than those listed in a Medication Guide. Do not use Mefloquine Hydrochloride Tablets for a condition for which it was not prescribed. Do not give mefloquine to other people, even if they have the same symptoms that you have. It may harm them.

This Medication Guide summarizes the most important information about mefloquine. If you would like more information, talk with your doctor. You can ask your pharmacist or doctor for information about mefloquine that is written for health professionals.

If you have any questions or would like more information about Mefloquine Hydrochloride Tablets, you can call West-ward Pharmaceutical Corp., the manufacturer of Mefloquine Hydrochloride Tablets, at 1-877-233-2001.

What are the ingredients in Mefloquine Hydrochloride Tablets?

Active ingredients: mefloquine hydrochloride

Inactive ingredients: colloidal silicon dioxide, corn starch, crospovidone, lactose monohydrate, lactose spray dried, magnesium stearate, microcrystalline cellulose, polysorbate 80, polyvinylpyrrolidone and talc.

This Medication Guide has been approved by the U.S. Food and Drug Administration.

Information Wallet Card
Mefloquine Hydrochloride Tablets
It is important that you read the entire Medication Guide for additional
information on Mefloquine Hydrochloride Tablets.
Carry this wallet card with you when you are taking Mefloquine Hydrochloride Tablets.

You need to take malaria prevention medicine before you travel to a malaria area, while you are in a malaria area, and after you return from a malaria area.

Mefloquine Hydrochloride Tablets can cause serious mental problems in some people. If you takeMefloquine Hydrochloride Tablets and you have sudden signs of serious mental problems (such as: severe anxiety, feelings of mistrust towards others, seeing or hearing things that are not there, depression, feeling restless, unusual behavior or feeling confused), you should contact a doctor right away as it may be necessary to stop taking Mefloquine Hydrochloride Tablets and take different medicine to prevent malaria.

Other side effects from Mefloquine Hydrochloride Tablets may include: convulsions, liver problems, and heart problems. The most common side effects of Mefloquine Hydrochloride Tablets include nausea, vomiting, diarrhea, abdominal pain, dizziness or loss of balance (vertigo) which may continue for months after Mefloquine Hydrochloride Tablets are stopped, headache, and sleeping problems (sleepiness, unable to sleep, bad dreams).

While you take Mefloquine Hydrochloride Tablets, do not take:

- Halofantrine (used to treat malaria)
- Ketoconazole (used for fungal infections)
- Quinine (Qualaquin) or quinidine (used to treat malaria or irregular heart beat)
- Chloroquine (Aralen) (used to treat malaria)

Avoid activities such as driving a car or using heavy machinery or other activities needing alertness and careful movements (fine motor coordination) until you know how Mefloquine Hydrochloride Tablets affect you.

Other medicines are approved in the United States for malaria prevention. However, not all malaria medicines work equally well in different malaria areas. Before you travel, talk to your doctor about your travel plans.

If you have any serious side effects, and cannot get another medicine, leave the malaria area and contact a doctor as soon as possible because leaving the malaria area may not protect you from getting malaria. You will still need to take a malaria prevention medicine.

Call your doctor for medical advice about side effects.

You may report side effects to FDA at 1-800-FDA-1088.

Card Revised: 03/10

Manufactured by:
West-ward Pharmaceutical Corp.
Eatontown, NJ 07724
Revised March 2010

PRINCIPAL DISPLAY PANEL

Repacked by:

H.J. Harkins Company, Inc.

Nipomo, CA 93444

NDC 0143-1282-22

Mefloquine Hydrochloride Tablet 250 mg